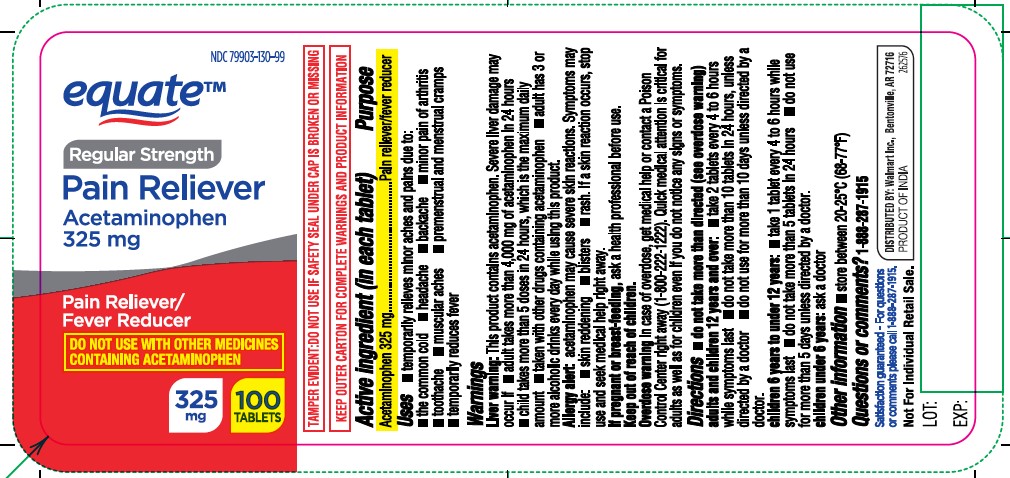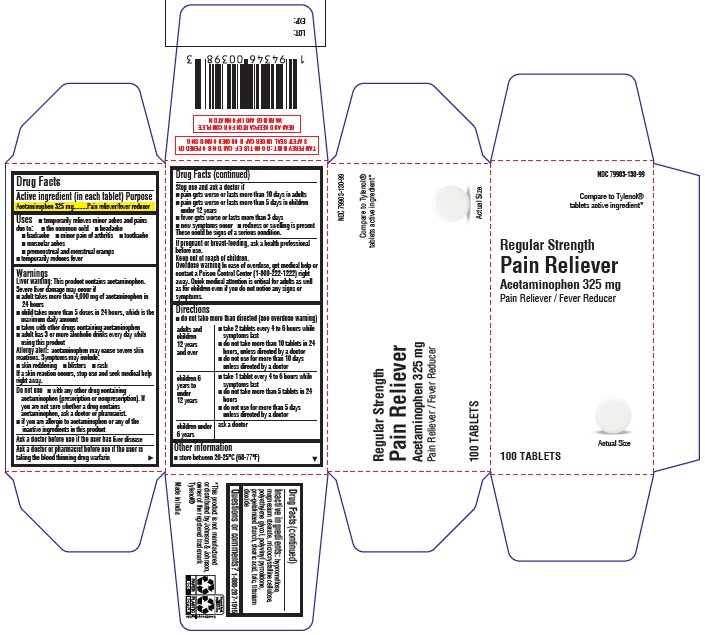 DRUG LABEL: Pain Reliever
NDC: 79903-130 | Form: TABLET, FILM COATED
Manufacturer: WAL-MART STORES INC
Category: otc | Type: HUMAN OTC DRUG LABEL
Date: 20260126

ACTIVE INGREDIENTS: ACETAMINOPHEN 325 mg/1 1
INACTIVE INGREDIENTS: TALC; TITANIUM DIOXIDE; HYPROMELLOSES; MAGNESIUM STEARATE; MICROCRYSTALLINE CELLULOSE; POLYETHYLENE GLYCOL, UNSPECIFIED; PYRROLIDONE; STARCH, CORN; STEARIC ACID

Pain Reliever

Active Ingredient (in each tablet)

Acetaminophen 325 mg

Purpose

Pain reliever/fever reducer

Uses

• temporarily relieves minor aches and pains due to: • the common cold • headache • backache • minor pain of arthritis • toothache • muscular aches • premenstrual and menstrual cramps • temporarily reduces fever

Warnings

Liver warning: This product contains acetaminophen. Severe liver damage may occur if you take
• more than 4,000 mg of acetaminophen in 24 hours • with other drugs containing acetaminophen • 3 or more alcoholic drinks every day while using this product.

Allergy alert: Acetaminophen may cause severe skin reactions. Symptoms may include: • skin reddening • blisters • rash. If a skin reaction occurs, stop use and seek medical help right away.

Do not use • with any other drug containing acetaminophen (prescription or non prescription). If you are not sure whether a drug contains acetaminophen, ask a doctor or pharmacist. • if you are allergic to acetaminophen or any of the inactive ingredients in this product

Ask a doctor before use if the user has liver disease

Ask a doctor or pharmacist before use if the user is taking the blood thinning drug warfarin

Stop use and ask a doctor if • pain gets worse or lasts more than 10 days • fever gets worse or lasts more than 3 days • new symptoms occur • redness or swelling is present. These could be signs of a serious condition.

PREGNANCY OR BREAST FEEDING

If pregnant or breast-feeding, ask a health professional before use.

Keep out of reach of children.

OVERDOSAGE

Overdose warning: In case of overdose, get medical help or contact a Poison Control Center right away. (1-800-222-1222) Quick medical attention is critical for adults as well as for children even if you do not notice any signs or symptoms.

Directions

do not take more than directed (see overdose warning)

adults & children 12 years & over | • take 2 tablets every 4 to 6 hours while symptoms last • do not take more than 10 tablets in 24 hours, unless directed by a doctor • do not use for more than 10 days unless directed by a doctor
children 6 years to under 12 years | • take 1 tablet every 4 to 6 hours while symptoms last • do not take more than 5 tablets in 24 hours • do not use for more than 5 days unless directed by a doctor
children under 6 years | ask a doctor

Other information

• store between 20–25°C (68–77°F)

Inactive ingredients

hypromellose, magnesium stearate, microcrystalline cellulose, polyethylene glycol, polyvinyl pyrrolidone, pre-gelatinized starch, stearic acid, talc, titanium dioxide

Questions or comments?

1-888-333-9792

Principal Display Panel

Label

Caton